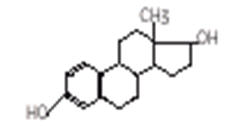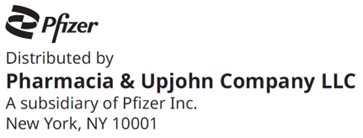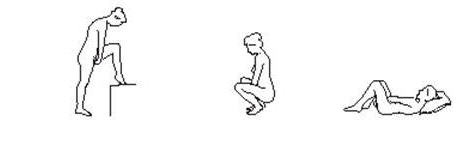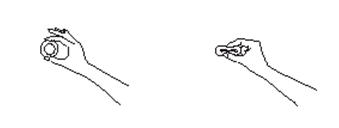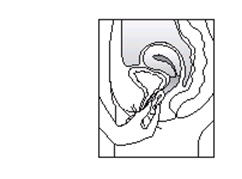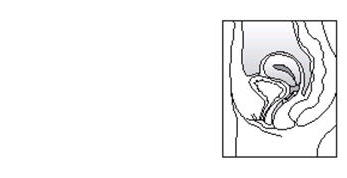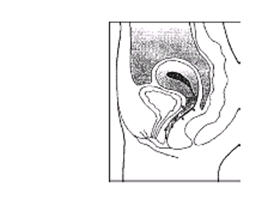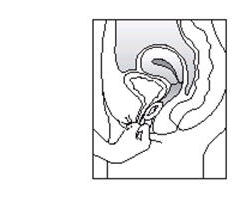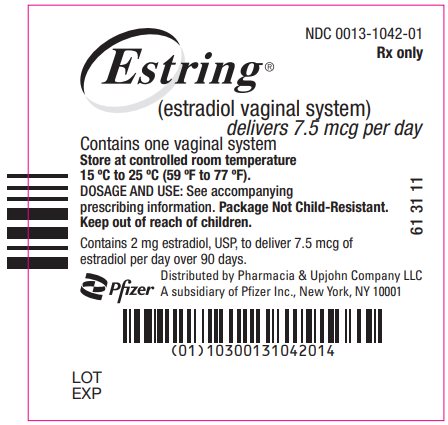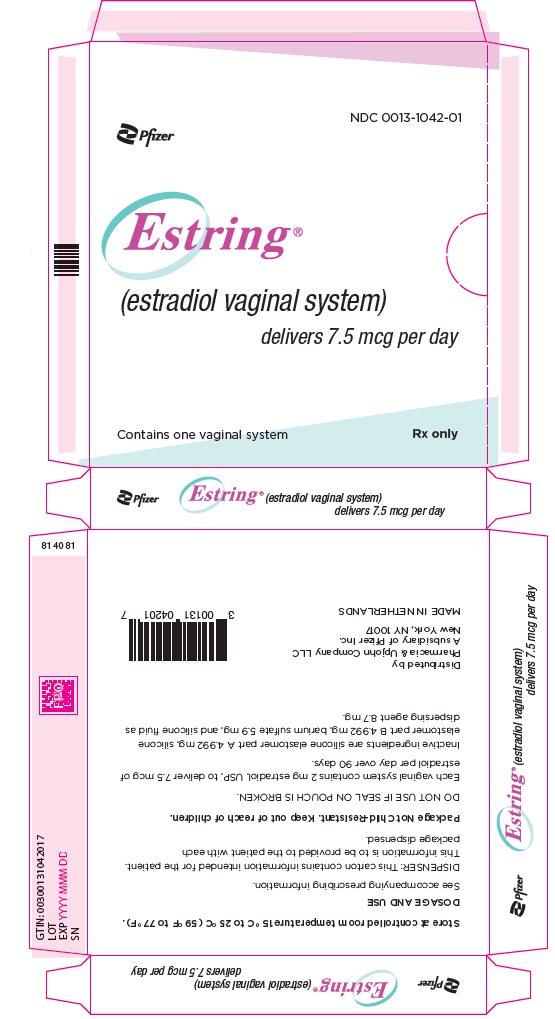 DRUG LABEL: Estring
NDC: 0013-1042 | Form: SYSTEM
Manufacturer: Pfizer Laboratories Div Pfizer Inc
Category: prescription | Type: HUMAN PRESCRIPTION DRUG LABEL
Date: 20260226

ACTIVE INGREDIENTS: ESTRADIOL 2 mg/1 1
INACTIVE INGREDIENTS: BARIUM SULFATE

ESTRING®
(estradiol vaginal system)

DESCRIPTION

ESTRING® (estradiol vaginal system) is a slightly opaque ring with a whitish core containing a drug reservoir of 2 mg estradiol. Estradiol, silicone polymers, barium sulfate and silicone fluid (as dispersing agent) are combined to form the ring. When placed in the vagina, ESTRING releases estradiol, approximately 7.5 mcg per day, in a consistent stable manner over 90 days. ESTRING has the following dimensions: outer diameter 55 mm; cross-sectional diameter 9 mm; core diameter 2 mm. One ESTRING should be inserted into the upper third of the vaginal vault, to be worn continuously for three months.

Estradiol is chemically described as estra-1, 3, 5(10)-triene-3, 17β-diol. The molecular formula of estradiol is C18H24O2 and the structural formula is:

The molecular weight of estradiol is 272.39.

CLINICAL PHARMACOLOGY

Endogenous estrogens are largely responsible for the development and maintenance of the female reproductive system and secondary sexual characteristics. Although circulating estrogens exist in a dynamic equilibrium of metabolic interconversions, estradiol is the principal intracellular human estrogen and is substantially more potent than its metabolites, estrone and estriol, at the receptor level.

The primary source of estrogen in normally cycling adult women is the ovarian follicle, which secretes 70 to 500 mcg of estradiol daily, depending on the phase of the menstrual cycle. After menopause, most endogenous estrogen is produced by conversion of androstenedione, secreted by the adrenal cortex, to estrone in the peripheral tissues. Thus, estrone and the sulfate conjugated form, estrone sulfate, are the most abundant circulating estrogens in postmenopausal women.

Estrogens act through binding to nuclear receptors in estrogen-responsive tissues. To date, two estrogen receptors have been identified. These vary in proportion from tissue to tissue.

Circulating estrogens modulate the pituitary secretion of the gonadotropins, luteinizing hormone (LH) and follicle stimulating hormone (FSH), through a negative feedback mechanism. Estrogens act to reduce the elevated levels of these hormones seen in postmenopausal women.

Pharmacokinetics

Absorption

Estrogens used in therapeutics are well absorbed through the skin, mucous membranes, and the gastrointestinal (GI) tract. The vaginal delivery of estrogens circumvents first-pass metabolism.

In a Phase I study of 14 postmenopausal women, the insertion of ESTRING (estradiol vaginal system) rapidly increased serum estradiol (E2) levels. The time to attain peak serum estradiol levels (Tmax) was 0.5 to 1 hour. Peak serum estradiol concentrations post-initial burst declined rapidly over the next 24 hours and were virtually indistinguishable from the baseline mean (range: 5 to 22 pg/mL). Serum levels of estradiol and estrone (E1) over the following 12 weeks during which the ring was maintained in the vaginal vault remained relatively unchanged (See Table 1).

The initial estradiol peak post-application of the second ring in the same women resulted in ~38 percent lower Cmax, apparently due to reduced systemic absorption via the treated vaginal epithelium. The relative systemic exposure from the initial peak of ESTRING accounted for approximately 4 percent of the total estradiol exposure over the 12-week period.

The release of estradiol from ESTRING was demonstrated in a Phase II study of 222 postmenopausal women who inserted up to four rings consecutively at three-month intervals. Systemic delivery of estradiol from ESTRING resulted in mean steady state serum estradiol estimates of 7.8, 7.0, 7.0, 8.1 pg/mL at weeks 12, 24, 36, and 48, respectively. Similar reproducibility is also seen in levels of estrone. The systemic exposure to estradiol and estrone was within the range observed in untreated women after the first eight hours.

In postmenopausal women, mean dose of estradiol systemically absorbed unchanged from ESTRING is ~8 percent [95 percent CI: 2.8–12.8 percent] of the daily amount released locally.

TABLE 1: PHARMACOKINETIC MEAN ESTIMATES FOLLOWING SINGLE ESTRING APPLICATION
Estrogen | Cmax (pg/mL) | Css–48 hr (pg/mL) | Css–4w (pg/mL) | Css–12w (pg/mL)
Estradiol (E2) | 63.2 [n=14] | 11.2 | 9.5 | 8.0
Baseline-adjusted E2 [Based on means] | 55.6 | 3.6 | 2.0 | 0.4
Estrone (E1) | 66.3 | 52.5 | 43.8 | 47.0
Baseline-adjusted E1 | 20.0 | 6.2 | -2.4 | 0.8

Distribution

The distribution of exogenous estrogens is similar to that of endogenous estrogens. Estrogens are widely distributed in the body and are generally found in higher concentrations in the sex hormone target organs. Estrogens circulate in the blood largely bound to sex hormone binding globulin (SHBG) and albumin.

Metabolism

Exogenous estrogens are metabolized in the same manner as endogenous estrogens. Circulating estrogens exist in a dynamic equilibrium of metabolic interconversions. These transformations take place mainly in the liver. Estradiol is converted reversibly to estrone, and both can be converted to estriol, which is a major urinary metabolite. Estrogens also undergo enterohepatic recirculation via sulfate and glucuronide conjugation in the liver, biliary secretion of conjugates into the intestine, and hydrolysis in the intestine followed by reabsorption. In postmenopausal women, a significant proportion of the circulating estrogens exist as sulfate conjugates, especially estrone sulfate, which serves as a circulating reservoir for the formation of more active estrogens.

Excretion

Estradiol, estrone, and estriol are excreted in the urine along with glucuronide and sulfate conjugates.

Special Populations

No pharmacokinetic studies were conducted with ESTRING in specific populations, including women with renal or hepatic impairment.

Drug Interactions

No formal drug interactions studies have been done with ESTRING.

In vitro and in vivo studies have shown that systemic estrogens are metabolized partially by cytochrome P450 3A4 (CYP3A4). Therefore, inducers or inhibitors of CYP3A4 may affect estrogen metabolism. Inducers of CYP3A4 such as St. John's Wort (Hypericum perforatum) preparations, phenobarbital, carbamazepine, and rifampin may reduce plasma concentrations of estrogens, possibly resulting in a decrease in systemic effects and/or changes in the uterine bleeding profile. Inhibitors of CYP3A4 such as erythromycin, clarithromycin, ketoconazole, itraconazole, ritonavir and grapefruit juice may increase plasma concentrations of estrogens and may result in side effects.

CLINICAL STUDIES

Effects on Vulvar and Vaginal Atrophy

Two controlled studies have demonstrated the efficacy of ESTRING (estradiol vaginal system) in the treatment of postmenopausal urogenital symptoms due to estrogen deficiency.

In a U.S. study where ESTRING was compared with conjugated estrogens vaginal cream, no difference in efficacy between the treatment groups was found with respect to improvement in the physician's global assessment of vaginal symptoms (83 percent and 82 percent of patients receiving ESTRING and cream, respectively) and in the patient's global assessment of vaginal symptoms (83 percent and 82 percent of patients receiving ESTRING and cream, respectively) after 12 weeks of treatment. In an Australian study, ESTRING was also compared with conjugated estrogens vaginal cream and no difference in the physician's assessment of improvement of vaginal mucosal atrophy (79 percent and 75 percent for ESTRING and cream, respectively) or in the patient's assessment of improvement in vaginal dryness (82 percent and 76 percent for ESTRING and cream, respectively) after 12 weeks of treatment.

In the U.S. study, symptoms of dysuria and urinary urgency improved in 74 percent and 65 percent, respectively, of patients receiving ESTRING as assessed by the patient. In the Australian study, symptoms of dysuria and urinary urgency improved in 90 percent and 71 percent, respectively, of patients receiving ESTRING as assessed by the patient.

In both studies, ESTRING and conjugated estrogens vaginal cream had a similar ability to reduce vaginal pH levels and to mature the vaginal mucosa (as measured cytologically using the maturation index and/or the maturation value) after 12 weeks of treatment. In supportive studies, ESTRING was also shown to have a similar significant treatment effect on the maturation of the urethral mucosa.

Endometrial overstimulation, as evaluated in non-hysterectomized patients participating in the U.S. study by the progestogen challenge test and pelvic sonogram, was reported for none of the 58 (0 percent) patients receiving ESTRING and 4 of the 35 patients (11 percent) receiving conjugated estrogens vaginal cream.

Of the U.S. women who completed 12 weeks of treatment, 95 percent rated product comfort for ESTRING as excellent or very good compared with 65 percent of patients receiving conjugated estrogens vaginal cream, 95 percent of ESTRING patients judged the product to be very easy or easy to use compared with 88 percent of cream patients, and 82 percent gave ESTRING an overall rating of excellent or very good compared with 58 percent for the cream.

Women's Health Initiative Trial with Oral Conjugated Estrogen

The Women’s Health Initiative (WHI) estrogen-alone trial enrolled predominantly healthy postmenopausal women to assess the risks and benefits of daily oral conjugated estrogen (CE) (0.625 mg)-alone compared to placebo in the prevention of certain chronic diseases. The primary endpoint was the incidence of coronary heart disease (CHD) (defined as nonfatal MI, silent MI and CHD death), with invasive breast cancer as the primary adverse outcome. A “global index” included the earliest occurrence of CHD, invasive breast cancer, stroke, PE, colorectal cancer, hip fracture, or death due to other cause.

The WHI oral CE-alone trial included 10,739 women (average 63 years of age, range 50 to 79; 75 percent White, 15 percent Black, 6 percent Hispanic, 4 other races), with an average follow-up of 7.1 years. The WHI oral CE-alone trial was stopped early because an increased risk of stroke was observed in the oral CE group. The stroke events were centrally adjudicated. The use of oral CE-alone, compared to placebo, increased the risk for ischemic stroke, and this excess risk was present in all subgroups of women examined.^1

No overall difference for centrally adjudicated primary CHD events (nonfatal MI, silent MI and CHD death) and invasive breast cancer incidence were seen in women who received oral CE-alone compared to those who received placebo after an average follow-up of 7.1 years.^1,2

The results of the WHI oral CE-alone trial are presented in Table 2.

TABLE 2: Relative Risk and Risk Difference Observed in the WHI Estrogen-Alone Trial at an Average of 7.1 Years of Follow-up [Adapted from 2013 WHI trial (CE n=5,310, placebo n=5,429). WHI publications can be viewed at www.nhlbi.nih.gov/whi.] , [Results are based on centrally adjudicated data.]
Event | Relative Ratio (95% CI) [In the WHI studies, hazard ratios were estimated using Cox proportional hazards models comparing treatment to placebo; however, they are described here as relative risks. Nominal confidence intervals unadjusted for multiple looks and multiple comparisons.] | Risk Difference (CE vs placebo/10,000 WYs)
CHD events; Nonfatal MI; CHD death | 0.94 (0.78-1.14); 0.97 (0.79-1.21); 1.00 (0.77-1.31) | -3 (55 vs 58); -1 (44 vs 45); 0 (29 vs 29)
All strokes | 1.35 (1.07-1.70) | 11 (45 vs 34)
Deep vein thrombosis [Not included in “global index.”] | 1.48 (1.06-2.07) | 7 (23 vs 15)
Pulmonary embolism | 1.35 (0.89-2.05) | 4 (14 vs 10)
Invasive breast cancer [Includes metastatic and non-metastatic breast cancer with the exception of in situ cancer.] | 0.79 (0.61-1.02) | -7 (28 vs 35)
Colorectal cancer | 1.15 (0.81-1.64) | 2 (17 vs 15)
Hip fracture | 0.67 (0.46-0.96) | -6 (13 vs 19)
Vertebral fractures | 0.64 (0.44-0.93) | -6 (12 vs 18)
Total fractures | 0.72 (0.64-0.80) | -61 (153 vs 214)
Overall mortality, [All deaths, except from breast or colorectal cancer, definite or probable CHD, PE or cerebrovascular disease.] | 1.03 (0.88-1.21) | 3 (80 vs 77)
Global index [A subset of the events was combined in a “global index,” defined as the earliest occurrence of CHD events, invasive breast cancer, stroke, PE, colorectal cancer, hip fracture, or death due to other causes.] | 1.03 (0.93-1.13) | 4 (208 vs 204)

Women's Health Initiative Memory Study with Oral Conjugated Estrogen

The Women’s Health Initiative Memory Study (WHIMS) estrogen-alone ancillary study of the WHI trial enrolled 2,947 predominantly healthy hysterectomized postmenopausal women 65 to 79 years of age and older to evaluate the effects of daily oral CE (0.625 mg)-alone on the incidence of probable dementia (primary outcome) compared to placebo. In the WHIMS, 45% of the women were 65 to 69 years of age; 36% were 70 to 74 years of age; and 19% were 75 years of age and older. Probable dementia as defined in this study included Alzheimer’s disease (AD), vascular dementia (VaD) and mixed type of dementia (having features of both AD and VaD). The most common classification of probable dementia in the treatment and placebo groups was AD.

In the WHIMS, after an average follow-up of 5.2 years, the relative risk of probable dementia for women in the oral CE-alone group versus the placebo group was 1.49 (95% CI, 0.83-2.66). The absolute risk of probable dementia for oral CE-alone group versus the placebo group was 37 versus 25 cases per 10,000 women-years.

Because WHIMS was conducted in women 65 to 79 years of age, it is unknown whether the findings in WHIMS apply to younger postmenopausal women.^3

INDICATIONS AND USAGE

ESTRING is indicated for the treatment of moderate to severe symptoms of vulvar and vaginal atrophy due to menopause.

CONTRAINDICATIONS

ESTRING is contraindicated in women with any of the following conditions:

1. Abnormal genital bleeding with unknown etiology.
2. Known or suspected estrogen-dependent neoplasia.
3. Active DVT, PE, or a history of these conditions.
4. Active arterial thromboembolic disease (for example, stroke and MI), or a history of these conditions.
5. Known anaphylactic reaction or angioedema or hypersensitivity to ESTRING.
6. Known liver impairment or disease.
7. Protein C, protein S, or antithrombin deficiency, or other known thrombophilic disorders.

WARNINGS

1. Endometrial Cancer with Unopposed Estrogen in Women with a Uterus

In ESTRING-treated menopausal women with a uterus with persistent or recurring abnormal genital bleeding of unknown etiology, perform adequate diagnostic measures, including directed or random endometrial sampling when indicated, to assess for endometrial cancer.

There is an increased risk of endometrial cancer with the use of systemic estrogens alone in women with a uterus. The reported endometrial cancer risk among unopposed systemic estrogen users is about 2 to 12 times greater than in non-users and appears dependent on duration of treatment and on estrogen dose. Most studies show no significant increased risk associated with the use of systemically administered estrogens for less than one year. The greatest risk appears to be associated with prolonged use, with increased risks of 15- to 24-fold for 5 to 10 years or more. This risk has been shown to persist for at least 8 to 15 years after systemic estrogen therapy is discontinued. There is no evidence that the use of natural estrogens results in a different endometrial risk profile than synthetic estrogens of equivalent estrogen dose.

Adding a progestogen to estrogen-alone therapy has been shown to reduce the risk of endometrial hyperplasia (possible precursor to endometrial cancer). There is, however, a different risk profile associated with the use of progestogens plus estrogens compared to estrogen-alone regimens.

2. Risks Associated with Concomitant Use of Estrogen Plus Progestogen

If ESTRING is administered with a progestogen, there are possible risks associated with the concomitant use of estrogen with progestogen that differ from those of estrogen-alone regimens. Refer to the prescribing information for progestogens indicated for the prevention of endometrial hyperplasia in nonhysterectomized women receiving estrogens for a discussion of the risks of estrogen and progestogen concomitant therapy.

3. Risks with Systemic Estrogen-Alone Therapy

Systemic absorption occurs with the use of ESTRING, although the exposure is generally lower than that of systemic estrogens indicated for vasomotor symptoms. As such, the relevance or extent of the following risks of systemic estrogens to ESTRING is not known. The following adverse reactions have been reported with systemic estrogen therapy:

Cardiovascular diseases: The Women’s Health Initiative (WHI) estrogen-alone trial reported increased risks of pulmonary embolism (PE), deep vein thrombosis (DVT), and stroke, in postmenopausal women (50 to 79 years of age, average age 63.4 years) during 7.2 years of treatment with daily oral conjugated estrogens (CE) [0.625 mg] relative to placebo. (See CLINICAL STUDIES.)

Breast cancer: In the WHI estrogen-alone trial, after an average follow-up of 7.1 years, daily oral CE-alone was not associated with an increased risk of invasive breast cancer. (See CLINICAL STUDIES.) However, a large meta-analysis including 24 prospective studies of postmenopausal women comparing current use of estrogen only products with use duration of 5 to 14 years (average of 9 years) versus never use reported a relative risk for breast cancer of 1.33 (95% CI, 1.28 to 1.38).

Ovarian cancer: A large meta-analysis including 17 prospective studies of postmenopausal women compared current use of estrogen-only products versus never user and reported a relative risk for ovarian cancer of 1.37 (95% CI 1.26, 1.50). The duration of hormone therapy use that was associated with an increased risk of ovarian cancer is unknown.^4

Others: gallbladder disease requiring surgery, severe hypercalcemia in women with breast cancer and metastases, retinal vascular thrombosis, substantial increases in blood pressure from idiosyncratic reactions, exacerbation of hypertriglyceridemia leading to pancreatitis, cholestatic jaundice, exacerbation of hypothyroidism, fluid retention, hypocalcemia, exacerbation of conditions including hereditary angioedema, asthma, diabetes mellitus, epilepsy, migraine, porphyria, systemic lupus erythematosus, and hepatic hemangiomas.

PRECAUTIONS

A. General

1. Location of ESTRING

Some women have experienced moving or gliding of ESTRING within the vagina. Instances of ESTRING being expelled from the vagina in connection with moving the bowels, strain, or constipation have been reported. If this occurs, ESTRING can be rinsed in lukewarm water and reinserted into the vagina by the patient.

2. Vaginal Irritation

ESTRING may not be suitable for women with narrow, short, or stenosed vaginas. Narrow vagina, vaginal stenosis, prolapse, and vaginal infections are conditions that make the vagina more susceptible to ESTRING-caused irritation or ulceration. Women with signs or symptoms of vaginal irritation should alert their physician.

3. Vaginal Infection

Vaginal infection is generally more common in postmenopausal women due to the lack of the normal flora of fertile women, especially lactobacillus, and the subsequent higher pH. Vaginal infections should be treated with appropriate antimicrobial therapy before initiation of ESTRING. If a vaginal infection develops during use of ESTRING, then ESTRING should be removed and reinserted only after the infection has been appropriately treated.

B. Patient Information

Physicians are advised to discuss the PATIENT INFORMATION leaflet with women for whom they prescribe ESTRING.

C. Laboratory Tests

Serum FSH and estradiol levels have not been shown to be useful in the management of moderate to severe symptoms of vulvar and vaginal atrophy.

D. Drug and Laboratory Test Interactions

1. Accelerated prothrombin time, partial thromboplastin time, and platelet aggregation time; increased platelet count; increased factors II, VII antigen, VIII antigen, VIII coagulant activity, IX, X, XII, VII-X complex, II-VII-X complex, and beta-thromboglobulin; decreased levels of anti-factor Xa and antithrombin III, decreased antithrombin III activity; increased levels of fibrinogen and fibrinogen activity; increased plasminogen antigen and activity.
2. Increased thyroid-binding globulin (TBG) levels leading to increased circulating total thyroid hormone levels, as measured by protein-bound iodine (PBI), T4 levels (by column or by radioimmunoassay) or T3 levels by radioimmunoassay. T3 resin uptake is decreased, reflecting the elevated TBG. Free T4 and free T3 concentrations are unaltered. Women on thyroid replacement therapy may require higher doses of thyroid hormone.
3. Other binding proteins may be elevated in serum, (i.e., corticosteroid binding globulin [CBG], sex hormone-binding globulin [SHBG]), leading to increased circulating corticosteroid and sex steroids, respectively. Free hormone concentrations, such as testosterone and estradiol, may be decreased. Other plasma proteins may be increased (angiotensinogen/renin substrate, alpha-1-antitrypsin, ceruloplasmin).
4. Increased plasma high-density (HDL) and HDL2 cholesterol subfraction concentrations, reduced low-density (LDL) cholesterol concentration, increased triglycerides levels.
5. Impaired glucose tolerance.

E. Carcinogenesis, Mutagenesis, and Impairment of Fertility

Long-term, continuous administration of natural and synthetic estrogens in certain animal species increases the frequency of carcinomas of the breast, uterus, cervix, vagina, testes and liver.

F. Pregnancy

ESTRING should not be used during pregnancy.

There appears to be little or no increased risk of birth defects in children born to women who have used estrogens as an oral contraceptive inadvertently during early pregnancy.

G. Nursing Mothers

ESTRING should not be used during lactation. Estrogen administration to nursing women has been shown to decrease the quantity and quality of the breast milk. Detectable amounts of estrogens have been identified in the breast milk of mothers receiving estrogens. Caution should be exercised when ESTRING is administered to a nursing woman.

H. Pediatric Use

ESTRING is not indicated in children. Clinical studies have not been conducted in the pediatric population.

I. Geriatric Use

There have not been sufficient numbers of geriatric patients involved in studies utilizing ESTRING to determine whether those over 65 years of age differ from younger subjects in their response to ESTRING.

The Women's Health Initiative Study

In the WHI estrogen-alone substudy (daily CE [0.625 mg]-alone versus placebo), there was a higher relative risk of stroke in women greater than 65 years of age. (See CLINICAL STUDIES.)

The Women's Health Initiative Memory Study

In the WHIMS ancillary studies of postmenopausal women 65 to 79 years of age, there was an increased risk of developing probable dementia in women who received oral CE-alone compared to those who received placebo. (See CLINICAL STUDIES.)

Since trial was conducted in women 65 to 79 years of age, it is unknown whether these findings apply to younger postmenopausal women. (See CLINICAL STUDIES.)

ADVERSE REACTIONS

See WARNINGS and PRECAUTIONS

Because clinical trials are conducted under widely varying conditions, adverse reaction rates observed in the clinical trials of a drug cannot be directly compared to rates in the clinical trials of another drug and may not reflect the rates observed in practice.

In the two ESTRING controlled studies, discontinuation of treatment due to an adverse event was required by 5.4 percent of patients receiving ESTRING and 3.9 percent of patients receiving conjugated estrogens vaginal cream. The most common reasons for withdrawal from ESTRING treatment due to an adverse event were vaginal discomfort and gastrointestinal symptoms.

The adverse events reported with a frequency of 3 percent or greater in the two pivotal controlled studies by patients receiving ESTRING or conjugated estrogens vaginal cream are listed in Table 3.

TABLE 3: Adverse Events Reported by 3 Percent or More of Patients Receiving Either ESTRING or Conjugated Estrogens Vaginal Cream in Two Pivotal Controlled Studies
ADVERSE EVENT | ESTRING (n = 257) % | Conjugated Estrogens Vaginal Cream (n = 129) %
Musculoskeletal
Back Pain | 6 | 8
Arthritis | 4 | 2
Arthralgia | 3 | 5
Skeletal Pain | 2 | 4
CNS/Peripheral Nervous System
Headache | 13 | 16
Psychiatric
Insomnia | 4 | 0
Gastrointestinal
Abdominal Pain | 4 | 2
Nausea | 3 | 2
Respiratory
Upper Respiratory Tract Infection | 5 | 6
Sinusitis | 4 | 3
Pharyngitis | 1 | 3
Urinary
Urinary Tract Infection | 2 | 7
Female Reproductive
Leukorrhea | 7 | 3
Vaginitis | 5 | 2
Vaginal Discomfort/Pain | 5 | 5
Vaginal Hemorrhage | 4 | 5
Asymptomatic Genital Bacterial Growth | 4 | 6
Breast Pain | 1 | 7
Resistance Mechanisms
Genital Moniliasis | 6 | 7
Body as a Whole
Flu-Like Symptoms | 3 | 2
Hot Flushes | 2 | 3
Allergy | 1 | 4
Miscellaneous
Family Stress | 2 | 3

Postmarketing Experience

Cases of toxic shock syndrome (TSS) have been reported in women using vaginal rings. TSS is a rare, but serious disease that may cause death. Warning signs of TSS include fever, nausea, vomiting, diarrhea, muscle pain, dizziness, faintness, or a sunburn-rash on face and body.

Vaginal erosion, vaginal ulceration, adherence of the vaginal ring to the vaginal wall:

- Cases of ring adherence to the vaginal wall, making ring removal difficult, have occurred. Some cases have required surgical removal of vaginal rings.
- Cases of vaginal erosion and vaginal ulceration that may manifest as vaginal irritation, erythema. abrasion or spotting have occurred.

Vaginal wall ulceration or erosion should be carefully evaluated. If an ulceration or erosion has occurred, consideration should be given to leaving the ring out and not replacing it until healing is complete in order to prevent the ring from adhering to the healing tissue.

Cases of bowel obstruction and vaginal ring use have been reported. Persistent abdominal complaints consistent with obstruction should be carefully evaluated.

Cases of hypersensitivity have been reported.

The following additional adverse events were reported at least once by patients receiving ESTRING in the worldwide clinical program, which includes controlled and uncontrolled studies. A causal relationship with ESTRING has not been established.

Body as a Whole: allergic reaction

CNS/Peripheral Nervous System: dizziness

Gastrointestinal: enlarged abdomen, vomiting

Metabolic/Nutritional Disorders: weight decrease or increase

Musculoskeletal: arthropathy (including arthrosis)

Psychiatric: depression, decreased libido, nervousness

Reproductive: breast engorgement, breast enlargement, intermenstrual bleeding, genital edema, vulval disorder

Skin/Appendages: pruritus, pruritus ani

Urinary: micturition frequency, urethral disorder

Vascular: thrombophlebitis

Vision: abnormal vision

OVERDOSAGE

Overdosage of estrogen may cause nausea, vomiting, breast tenderness, abdominal pain, drowsiness and fatigue, and withdrawal bleeding may occur in women. Treatment of overdose consists of discontinuation of ESTRING together with institution of appropriate symptomatic care.

DOSAGE AND ADMINISTRATION

One ESTRING (estradiol vaginal system) is to be inserted as deeply as possible into the upper one-third of the vaginal vault. The ring is to remain in place continuously for three months, after which it is to be removed and, if appropriate, replaced by a new ring.

Should the ring be removed or fall out at any time during the 90-day treatment period, the ring should be rinsed in lukewarm water and re-inserted by the patient, or, if necessary, by a physician or nurse.

Retention of the ring for greater than 90 days does not represent overdosage but will result in progressively greater underdosage with the attendant risk of loss of efficacy and increasing risk of vaginal infections and/or erosions.

Instructions for Use

ESTRING (estradiol vaginal system) insertion

The ring should be pressed into an oval and inserted into the upper third of the vaginal vault. The exact position is not critical. When ESTRING is in place, the patient should not feel anything. If the patient feels discomfort, ESTRING is probably not far enough inside. Gently push ESTRING further into the vagina.

ESTRING use

ESTRING should be left in place continuously for 90 days and then, if continuation of therapy is deemed appropriate, replaced by a new ESTRING.

The patient should not feel ESTRING when it is in place and it should not interfere with sexual intercourse. Straining at defecation may make ESTRING move down in the lower part of the vagina. If so, it may be pushed up again with a finger.

If ESTRING is expelled totally from the vagina, it should be rinsed in lukewarm water and reinserted by the patient (or doctor/nurse if necessary).

ESTRING removal

ESTRING may be removed by hooking a finger through the ring and pulling it out.

For patient instructions, see Patient Information.

HOW SUPPLIED

Each ESTRING (estradiol vaginal system) contains 2 mg estradiol to deliver 7.5 mcg of estradiol per day over 90 days, and is individually packaged in a heat-sealed rectangular pouch consisting of three layers, from outside to inside: polyester, aluminum foil, and low-density polyethylene, respectively. The pouch is provided with a tear-off notch on one side.

NDC 0013-1042-01 ESTRING (estradiol vaginal system) delivers 7.5 mcg per day – one vaginal system (contains 2 mg estradiol to deliver 7.5 mcg of estradiol per day over 90 days).

STORAGE

Store at controlled room temperature 15° to 25 °C (59 °F to 77 °F).

REFERENCES

1. Manson, J. E., et al Menopausal hormone therapy and health outcomes during the intervention and extended poststopping phases of the Women's Health Initiative randomized trials. JAMA, 310(13): 1353–1368 (2013). https://doi.org/10.1001/jama.2013.278040.
2. Anderson GL, et al; Women's Health Initiative Steering Committee. Effects of conjugated equine estrogen in postmenopausal women with hysterectomy: the Women's Health Initiative randomized controlled trial. JAMA. 2004 Apr 14;291(14):1701-12. doi: 10.1001/jama.291.14.1701. PMID: 15082697.
3. Espeland MA, Rapp SR, Shumaker SA, Brunner R, Manson JE, Sherwin BB, Hsia J, Margolis KL, Hogan PE, Wallace R, Dailey M, Freeman R, Hays J; Women's Health Initiative Memory Study. Conjugated equine estrogens and global cognitive function in postmenopausal women: Women's Health Initiative Memory Study. JAMA. 2004 Jun 23;291(24):2959-68. doi: 10.1001/jama.291.24.2959. PMID: 15213207.
4. Collaborative Group on Epidemiological Studies of Ovarian Cancer; Beral V, Gaitskell K, Hermon C, Moser K, Reeves G, Peto R. Menopausal hormone use and ovarian cancer risk: individual participant meta-analysis of 52 epidemiological studies. Lancet. 2015 May 9;385(9980):1835-42. doi: 10.1016/S0140-6736(14)61687-1. Epub 2015 Feb 13. PMID: 25684585; PMCID: PMC4427760.

Rx only

LAB-1532-4.0
Revised 2/2026

PATIENT INFORMATION

ESTRING
(estradiol vaginal system)

Read this Patient Information before you start using ESTRING and each time you get a refill. There may be new information. This information does not take the place of talking to your healthcare provider about your menopausal symptoms or your treatment.

What is ESTRING?

ESTRING (estradiol vaginal system) is an off-white, soft, flexible ring with a center that contains 2 mg of estradiol (an estrogen hormone). ESTRING releases estradiol into the vagina in a consistent, stable manner for 90 days. The soft, flexible ring is placed in the upper third of the vagina (by the physician or the patient). ESTRING should be removed after 90 days of continuous use. If continuation of therapy is indicated, the flexible ring should be replaced.

What is ESTRING used for?

ESTRING is used after menopause to treat moderate to severe menopausal changes in and around the vagina.

You and your healthcare provider should talk regularly about whether you still need treatment with ESTRING to control these problems.

Who should not use ESTRING?

Do not start using ESTRING if you:

- have unusual vaginal bleeding
Vaginal bleeding after menopause may be a warning sign of cancer of the uterus (womb). Your healthcare provider should check any unusual vaginal bleeding to find out the cause.
- currently have or have had certain cancers
Estrogens may increase the chance of getting certain types of cancers. If you have or had an estrogen-dependent cancer, talk with your healthcare provider about whether you should use ESTRING.
- had a stroke or heart attack
- currently have or have had blood clots
- currently have liver problems
- have been diagnosed with a bleeding disorder
- are allergic to ESTRING or any of its ingredients
See the list of ingredients in ESTRING at the end of this leaflet.
- think you may be pregnant
ESTRING is not for pregnant women. If you think you may be pregnant, you should have a pregnancy test and know the results. Do not use ESTRING if the test is positive and talk to your healthcare provider.

What should I tell my healthcare provider before I use ESTRING?
Before you use ESTRING, tell your healthcare provider if you:

- have any unusual vaginal bleeding
Vaginal bleeding after menopause may be a warning sign of cancer of the uterus (womb). Your healthcare provider should check any unusual vaginal bleeding to find out the cause.
- have any other medical conditions
Your healthcare provider may need to check you more carefully if you have certain conditions, such as asthma (wheezing), epilepsy (seizures), diabetes, migraine, endometriosis, lupus, angioedema (swelling of face and tongue), or problems with your heart, liver, thyroid, kidneys, or have high calcium levels in your blood.
- are going to have surgery or will be on bed rest
Your healthcare provider will let you know if you need to stop using ESTRING.
- are breast feeding
The hormone in ESTRING can pass into your breast milk.

Tell your healthcare provider about all the medicines you take including prescription and nonprescription medicines, vitamins, and herbal supplements. Some medicines may affect how ESTRING works. ESTRING may also affect how your other medicines work.

What are the possible side effects of ESTRING?

If you experience any of the following side-effects, immediately remove ESTRING if possible and contact your healthcare provider. If you experience difficulty or pain when trying to remove the ring please do not continue and contact your healthcare provider:

- Cases of toxic shock syndrome (TSS) have been reported in women using vaginal rings. Toxic shock syndrome is a rare but serious illness caused by a bacterial infection. Symptoms of TSS include fever, nausea, vomiting, diarrhea, muscle pain, dizziness, faintness, or a sunburn-like rash on face and body.
- Cases of the vaginal ring becoming attached to the vaginal wall, making ring removal difficult, have occurred. Some women have needed surgery to remove vaginal rings.
- Cases of erosion (wearing away) and ulceration (holes) of the vaginal lining have also occurred. Symptoms of vaginal erosion and ulceration can include vaginal pain or soreness, vaginal bleeding, and redness, swelling, or scrapes in the vagina.
- Cases of bowel obstruction have been reported.
- Severe allergic reactions have been reported including skin rash, giant hives, swelling of the eyelids, face, lips, tongue or throat.

The most frequently reported side effect with ESTRING use is increased vaginal secretions. Many of these vaginal secretions are like those that occur normally prior to menopause and indicate that ESTRING is working. Vaginal secretions that are associated with a bad odor, vaginal itching, or other signs of vaginal infection are NOT normal and may indicate a risk or a cause for concern. Other side effects may include vaginal discomfort, abdominal pain, or genital itching.

What are the possible side effects of estrogens?

Side effects are grouped by how serious they are and how often they happen when you are treated.

Serious, but less common side effects include:

- heart attack
- stroke
- blood clots
- dementia
- breast cancer
- cancer of the lining of the uterus (womb)
- cancer of the ovary
- high blood pressure
- high blood sugar
- gallbladder disease
- liver problems
- changes in your thyroid hormone levels
- enlargement of benign tumors of the uterus ("fibroids")

Call your healthcare provider right away if you get any of the following warning signs or any other unusual symptoms that concern you:

- new breast lumps
- unusual vaginal bleeding
- changes in vision or speech
- sudden new severe headaches
- severe pains in your chest or legs with or without shortness of breath, weakness and fatigue
- memory loss or confusion

Less serious, but common side effects include:

- headache
- breast pain
- irregular vaginal bleeding or spotting
- stomach or abdominal cramps, bloating
- nausea and vomiting
- fluid retention
- vaginal yeast infection

These are not all the possible side effects of ESTRING. For more information, ask your healthcare provider or pharmacist for advice about side effects. Tell your healthcare provider if you have any side effect that bothers you or does not go away.

Call your healthcare provider for medical advice about side effects. You may report side effects to FDA at 1-800-FDA-1088. You may report side effects to Pfizer at 1-800-438-1985.

What can I do to lower my chances of getting a serious side effect with ESTRING?

- Follow carefully the instructions for use.
- Talk with your healthcare provider regularly about whether you should continue using ESTRING.
- See your healthcare provider right away if you get vaginal bleeding while using ESTRING.
- If you have fever, nausea, vomiting, diarrhea, muscle pain, dizziness, faintness, or a sunburn-like rash on face and body, remove ESTRING and contact your healthcare provider.
- Contact your healthcare provider if you have difficulty removing the vaginal ring.
- Have a breast exam and mammogram (breast X-ray) every year unless your healthcare provider tells you something else. If members of your family have had breast cancer or if you have ever had breast lumps or an abnormal mammogram, you may need to have breast examinations more often.
- If you have high blood pressure, high cholesterol (fat in the blood), diabetes, are overweight, or if you use tobacco, you may have higher chances for getting heart disease. Ask your healthcare provider for ways to lower your chances for getting heart disease.

General information about safe and effective use of ESTRING

Medicines are sometimes prescribed for conditions that are not mentioned in patient information leaflets. Do not use ESTRING for conditions for which it was not prescribed. Do not give ESTRING to other people, even if they have the same symptoms you have. It may harm them.

Keep ESTRING out of the reach of children.

This leaflet provides a summary of the most important information about ESTRING. If you would like more information, talk with your healthcare provider or pharmacist. You can ask for information about ESTRING that is written for health professionals. You can get more information by calling the toll free number 1-888-691-6813.

What are the ingredients in ESTRING?

ESTRING (estradiol vaginal system) is a slightly opaque ring with a whitish core containing a drug reservoir of 2 mg estradiol (an estrogen hormone). Estradiol, silicone polymers, barium sulfate and silicone fluid (as dispersing agent) are combined to form the ring.

Storage: Store at controlled room temperature 15° to 25 °C (59 °F to 77 °F).

INSTRUCTIONS FOR USE

How should I use ESTRING?

ESTRING is a local estrogen therapy used after menopause to treat moderate to severe menopausal changes in and around the vagina. ESTRING PROVIDES RELIEF OF LOCAL SYMPTOMS OF MENOPAUSE ONLY.

Estrogens should be used only as long as needed. You and your healthcare provider should talk regularly (for example, every 3 to 6 months) about whether you still need treatment with ESTRING.

ESTRING INSERTION

ESTRING can be inserted and removed by you or your doctor or healthcare provider. To insert ESTRING yourself, choose the position that is most comfortable for you: standing with one leg up, squatting, or lying down.

1. After washing and drying your hands, remove ESTRING from its pouch using the tear-off notch on the side. (Since the ring becomes slippery when wet, be sure your hands are dry before handling it.)
2. Hold ESTRING between your thumb and index finger and press the opposite sides of the ring together as shown.
3. Gently push the compressed ring into your vagina as far as you can.

ESTRING PLACEMENT

The exact position of ESTRING is not critical, as long as it is placed in the upper third of the vagina.

When ESTRING is in place, you should not feel anything. If you feel uncomfortable, ESTRING is probably not far enough inside. Use your finger to gently push ESTRING further into your vagina.

There is no danger of ESTRING being pushed too far up in the vagina or getting lost. ESTRING can only be inserted as far as the end of the vagina, where the cervix (the narrow, lower end of the uterus) will block ESTRING from going any further (See diagram of Female Anatomy).

ESTRING USE

Once inserted, ESTRING should remain in place in the vagina for 90 days.

Most women and their partners experience no discomfort with ESTRING in place during intercourse, so it is NOT necessary that the ring be removed. If ESTRING should cause you or your partner any discomfort, you may remove it prior to intercourse (See ESTRING Removal, below). Be sure to reinsert ESTRING as soon as possible afterwards.

ESTRING may slide down into the lower part of the vagina as a result of the abdominal pressure or straining that sometimes accompanies constipation. If this should happen, gently guide ESTRING back into place with your finger.

There have been rare reports of ESTRING falling out in some women following intense straining or coughing. If this should occur, simply wash ESTRING with lukewarm (NOT hot) water and reinsert it.

ESTRING DRUG DELIVERY

Once in the vagina, ESTRING begins to release estradiol immediately. ESTRING will continue to release a low, continuous dose of estradiol for the full 90 days it remains in place.

It will take about 2 to 3 weeks to restore the tissue of the vagina and urinary tract to a healthier condition and to feel the full effect of ESTRING in relieving vaginal and urinary symptoms. If your symptoms persist for more than a few weeks after beginning ESTRING therapy, contact your doctor or healthcare provider.

One of the most frequently reported effects associated with the use of ESTRING is an increase in vaginal secretions. These secretions are like those that occur normally prior to menopause and indicate that ESTRING is working. However, if the secretions are associated with a bad odor or vaginal itching or discomfort, be sure to contact your doctor or healthcare provider.

ESTRING REMOVAL

After 90 days there will no longer be enough estradiol in the ring to maintain its full effect in relieving your vaginal or urinary symptoms. ESTRING should be removed at that time and replaced with a new ESTRING, if your doctor determines that you need to continue your therapy.

To remove ESTRING:

1. Wash and dry your hands thoroughly.
2. Assume a comfortable position, either standing with one leg up, squatting, or lying down.
3. Loop your finger through the ring and gently pull it out.
4. Discard the used ring in a waste receptacle. (Do not flush ESTRING.)

If you have any additional questions about removing ESTRING, contact your doctor or healthcare provider.

LAB-1533-3.0
Revised 2/2026

PRINCIPAL DISPLAY PANEL - 2 mg Pouch Label

NDC 0013-1042-01
Rx only

Estring®
(estradiol vaginal system)
delivers 7.5 mcg per day

Contains one vaginal system
Store at controlled room temperature
15 ºC to 25 ºC (59 ºF to 77 ºF).
DOSAGE AND USE: See accompanying
prescribing information. Package Not Child-Resistant.
Keep out of reach of children.

Contains 2 mg estradiol, USP, to deliver 7.5 mcg of
estradiol per day over 90 days.

61 31 11

Pfizer

Distributed by Pharmacia & Upjohn Company LLC

A subsidiary of Pfizer Inc., New York, NY 10001

LOT
EXP

PRINCIPAL DISPLAY PANEL - 2 mg Pouch Carton

NDC 0013-1042-01

Pfizer

Estring®

(estradiol vaginal system)
delivers 7.5 mcg per day

Contains one vaginal system

Rx only